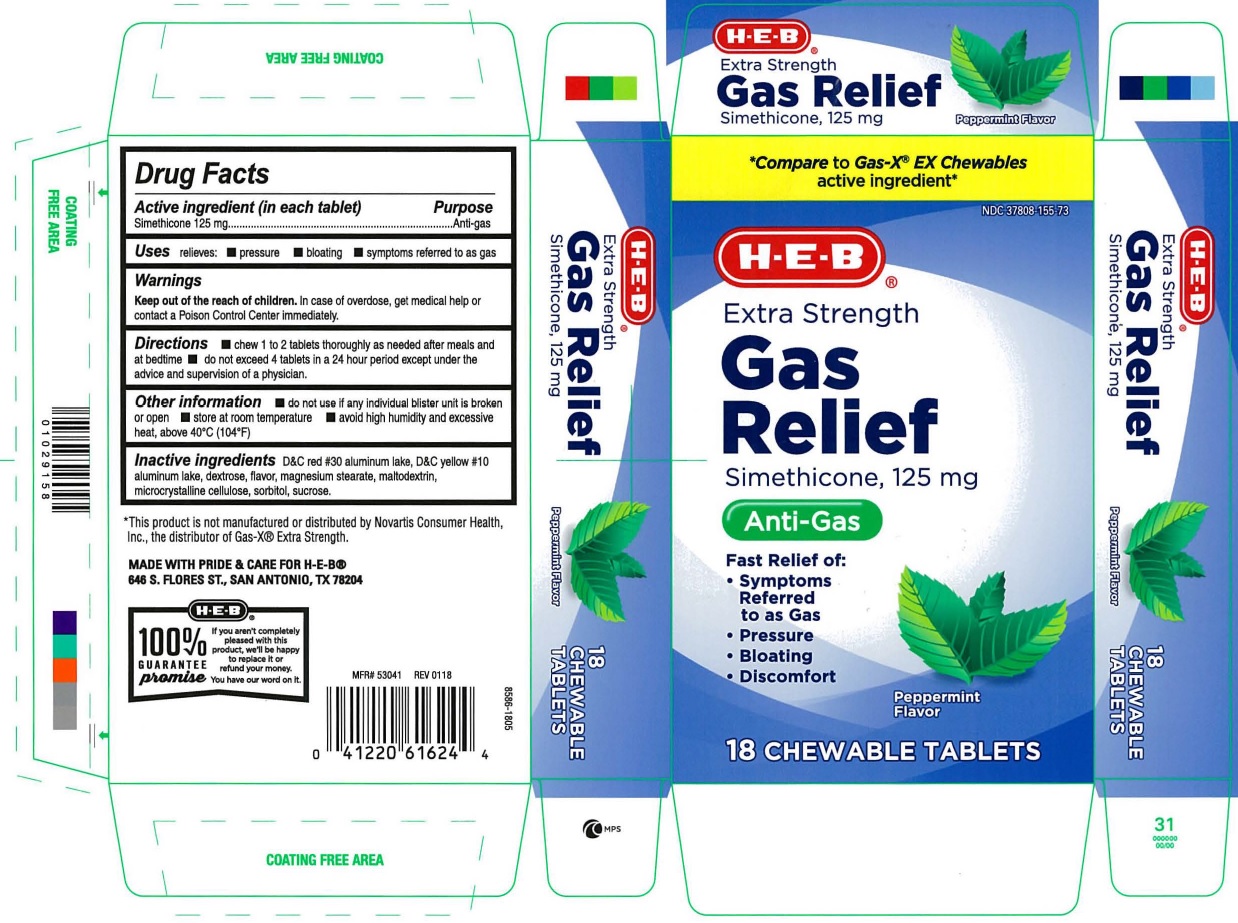 DRUG LABEL: HEB Gas Relief Extra Strength Peppermint
NDC: 37808-155 | Form: TABLET, CHEWABLE
Manufacturer: H E B
Category: otc | Type: Human OTC Drug Label
Date: 20250120

ACTIVE INGREDIENTS: DIMETHICONE 125 mg/1 1
INACTIVE INGREDIENTS: D&C RED NO. 30; MAGNESIUM STEARATE; CELLULOSE, MICROCRYSTALLINE; SORBITOL; SUCROSE; MALTODEXTRIN; D&C YELLOW NO. 10; DEXTROSE, UNSPECIFIED FORM

HEB Extra Strength Gas Relief Tablets

ACTIVE INGREDIENT(in each tablet)

Simethicone 125 mg

PURPOSE

Anti-gas

USE(S)

relieves:

- pressure
- bloating
- symptoms referred to as gas

WARNINGS

.

KEEP OUT OF REACH OF CHILDREN

In case of overdose, get medical help or contact a poison control center immediately.

DIRECTIONS

- chew 1 to 2 tablets thoroughly as needed after meals and at bedtime
- do not exceed 4 tablets in a 24 hour period except under the advice and supervision of a physician

OTHER INFORMATION

- do not use if any individual blister unit is broken or open
- store at room temperature
- avoid high humidity and excessive heat, above 40ºC (104ºF)

INACTIVE INGREDIENTS

D&C red # 30 aluminum lake, D&C yellow # 10 aluminum lake, dextrose, flavor, magnesium stearate, maltodextrin, microcrystalline cellulose, sorbitol, sucrose

PRINCIPAL DISPLAY PANEL

*Compare to Gas-X® EX chewables active ingredient
NDC 37808-155-73
HEB
Extra strength
Gas
Relief
Simethicone 125 mg
Anti-Gas
Fast Relief of:

- Symptoms Referred to as Gas
- Discomfort
- Pressure
- Bloating

Peppermint Flavor

18 chewable tablets